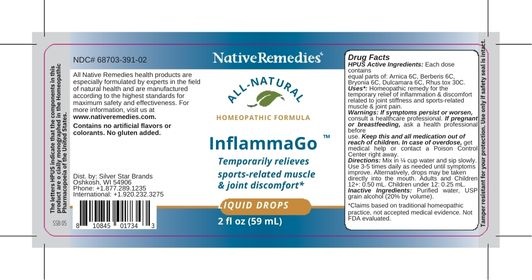 DRUG LABEL: NativeRemedies InflammaGo
NDC: 68703-391 | Form: LIQUID
Manufacturer: Silver Star Brands
Category: homeopathic | Type: HUMAN OTC DRUG LABEL
Date: 20250101

ACTIVE INGREDIENTS: BRYONIA ALBA ROOT 6 [hp_C]/59 mL; BERBERIS VULGARIS FRUIT 6 [hp_C]/59 mL; TOXICODENDRON RADICANS LEAF 30 [hp_C]/59 mL; ARNICA MONTANA 6 [hp_C]/59 mL; SOLANUM DULCAMARA STEM 6 [hp_C]/59 mL
INACTIVE INGREDIENTS: WATER; ALCOHOL

NativeRemedies® InflammaGo™

HPUS Active Ingredients: Each dose contains equal parts of: Arnica 6C, Berberis 6C, Bryonia 6C, Dulcamara 6C, Rhus tox 30C.

The letters HPUS indicated that the components in this product are officially monographed in the Homeopathic Pharmacopoeia of the United States.

Uses*

Uses*: Homeopathic remedy for the temporary relief of inflammation & discomfort related to joint stiffness and sports-relted muscle & joint pain.

*Claims based on traditional homeopathic practice, not accepted medical evidence. Not FDA evaluated.

Warnings

Warnings: If symptoms persist or worsen, consult a healthcare professional. If pregnant or breastfeeding, ask a health professional before use. Keep this and all medication out of reach of children. In case of overdose, get medical help or contact a Poison Control Center right away.

Directions

Directions: Mix in 1/4 cup water and sip slowly. Use 3-5 times daily as needed until symptoms improve. Alternatively, drops may be taken directly into the mouth. Adults and Children 12+: 0.50 mL. Children under 12: 0.25 mL.

OTHER SAFETY INFORMATION

Contains no artificial flavors or colorants. No gluten added.

Tampler resistant for your protection. Use only if safety seal is intact.

Inactive Ingredients

Inactive Ingredients: Purified water, USP grain alcohol (20% by volume).

KEEP OUT OF REACH OF CHILDREN

Keep this and all medication out of reach of children. In case of oversose, get medical help or contact a Poison Control Center right away.

PREGNANCY OR BREAST FEEDING

If pregnant or breastfeeding, ask a health professional before use.

PURPOSE

Temporarily relieves sports-related muscle & joint discomfort.